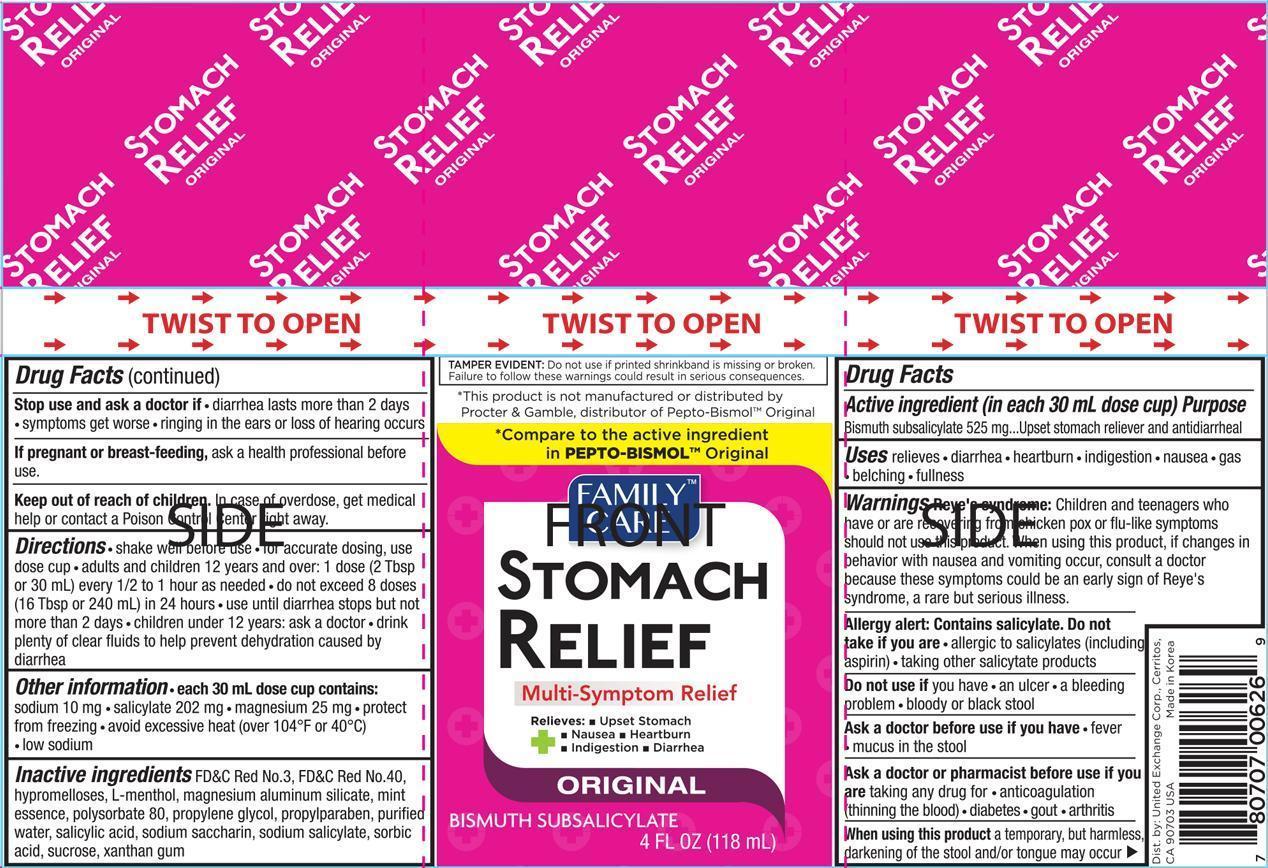 DRUG LABEL: Family Care Stomach Relief
NDC: 65923-626 | Form: LIQUID
Manufacturer: United Exchange Corp.
Category: otc | Type: HUMAN OTC DRUG LABEL
Date: 20150731

ACTIVE INGREDIENTS: BISMUTH SUBSALICYLATE 1050 mg/30 mL
INACTIVE INGREDIENTS: FD&C RED NO. 3; FD&C RED NO. 40; HYPROMELLOSES; MENTHOL; MAGNESIUM ALUMINUM SILICATE; POLYSORBATE 80; PROPYLENE GLYCOL; PROPYLPARABEN; WATER; SALICYLIC ACID; SODIUM SALICYLATE; SORBIC ACID; SUCROSE; XANTHAN GUM

Active ingredient (in each 30 mL dose cup) Purpose

Bismuth subsalicylate 525 mg..........................Upset stomach reliever and antidiarrheal

Uses

relieves

- diarrhea
- heartburn
- indigestion
- nausea
- gas
- belching
- fullness

Warnings

Reye's syndrome: children and teenagers who have or are recovering from chicken pox or flu-like symptoms should not use this product. When using this product, if changes in behavior with nausea and vomiting occur, consult a doctor because these symptoms could be an early sign of Reye's syndrome, a rare but serious illness.

Allergy alert: Contains salicylate. Do not take if you are

- allergic to salicylates (including aspirin)
- taking other salicytate products

Do not use if you have

- an ulcer
- a bleeding problem
- bloody or black stool

Ask a doctor before use if you have

- fever
- mucus in the stool

Ask a doctor before use if you are taking any drug for

- anticoagulation (thinning the blood)
- diabetes
- gout
- arthritis

When using this product a temporary, but harmless, darkening of the stool and/or tongue may occur

Stop use and ask a doctor if

- diarrhea lasts more than 2 days
- symptoms get worse
- ringing in the ears or loss of hearing occurs

PREGNANCY OR BREAST FEEDING

If pregnant or breast-feeding, ask a health professional before use.

Keep out of reach of children. In case of overdose, get medical help or contact a Poison Control Center right away.

Directions

- shake well before use
- for accurate dosing, use dose cup
- adults and children 12 years and over: 1 dose (2 Tbsp or 30 mL) every 1/2 to 1 hour as needed
- do not exceed 8 doses (16 Tbsp or 240 mL) in 24 hours
- use until diarrhea stops but not more than 2 days
- children under 12 years: ask a doctor
- drink plenty of clear fluids to help prevent dehydration caused by diarrhea

Other information

- each 30 mL dose cup contains: sodium 10 mg
- salicylate 202 mg
- magnesium 25 mg
- protect from freezing
- avoid excessive heat (over 104° or 40°C)
- low sodium

Inactive ingredients

FD&C Red No. 3, FD&C Red No. 40, hypromelloses, L-menthol, magnesium aluminum silicate, mint essence, polysorbate 80, propylene glycol, propylparaben, purified water, salicylic acid, sodium saccharin, sodium salicylate, sorbic acid, sucrose, xanthan gum

DOSAGE AND ADMINISTRATION

Distributed by:

United Exchange Corp.

Cerritos, CA 90703 USA

Made in Korea